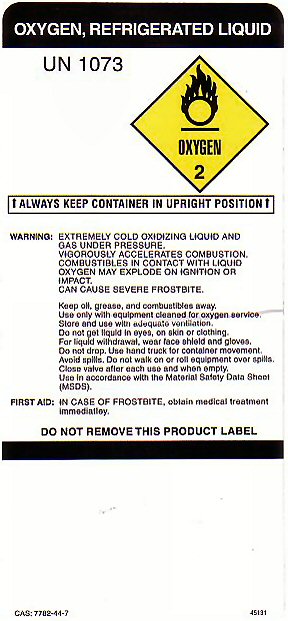 DRUG LABEL: OXYGEN
NDC: 68698-001 | Form: GAS
Manufacturer: Oxygen Plus LLC
Category: prescription | Type: HUMAN PRESCRIPTION DRUG LABEL
Date: 20100101

ACTIVE INGREDIENTS: OXYGEN 99 L/100 L

OXYGEN REFRIGERATED LIQUID LABEL

OXYGEN REFRIGERATED LIQUID UN 1073 OXYGEN-2 ALWAYS KEEP CONTAINER IN UPRIGHT POSITION WARNING: EXTREMELY COLD OXIDIZING LIQUID AND GAS UNDER PRESSURE VIGOROUSLY ACCELERATES COMBUSTION COMBUSTIBLES IN CONTACT WITH LIQUID OXYGEN MAY EXPLODE ON IGNITION OR IMPACT. CAN CAUSE SEVERE FROSTBITE. KEEP OIL GREASE AND COMBUSTIBLES AWAY. USE ONLY WITH EQUIPMENT CLEANED FOR OXYGEN SERVICE STORE AND USE WITH ADEQUATE VENTILATION DO NOT GET LIQUID IN EYES, ON SKIN OR CLOTHING FOR LIQUID WITHDRAWAL, WEAR FACE SHIELD AND GLOVES DO NOT DROP USE HAND TRUCK FOR CONTAINER MOVEMENT. AVOID SPILLS DO NOT WALK ON OR ROLL EQUIPMENT OVER SPILLS. CLOSE VALVE AFTER EACH USE AND WHEN EMPTY. USE IN ACCORDANCE WITH THE MATERIAL SAFETY DATA SHEET (MSDS) FIRST AID: IN CASE OF FROSTBITE OBTAIN MEDICAL TREATMENT IMMEDIATELY. DO NOT REMOVE THIS PRODUCT LABEL. CAS 7782-44-7